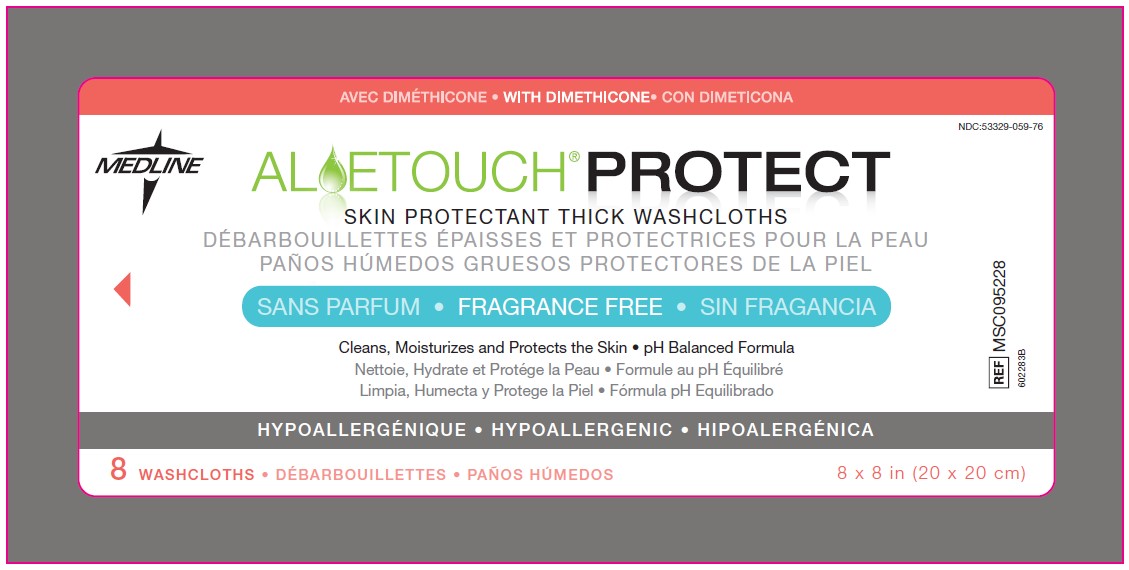 DRUG LABEL: Aloetouch Protect
NDC: 53329-059 | Form: CLOTH
Manufacturer: Medline Industries, LP
Category: otc | Type: HUMAN OTC DRUG LABEL
Date: 20260130

ACTIVE INGREDIENTS: DIMETHICONE 3.2 g/100 mL
INACTIVE INGREDIENTS: ALOE VERA LEAF; BENZALKONIUM CHLORIDE; CITRIC ACID MONOHYDRATE; COCAMIDOPROPYL PG-DIMONIUM CHLORIDE PHOSPHATE; EDETATE DISODIUM; LINOLEAMIDOPROPYL PG-DIMONIUM CHLORIDE PHOSPHATE; SODIUM BENZOATE; POLYSORBATE 20; WATER

059 Remedy Essentials Skin Protectant Wipes

Active ingredient

Dimethicone 3.2% w/v

Purpose

Skin Protectant

Uses

- temporarily protects and helps relieve chapped or cracked skin
- protects minor skin irritation associated with perineal dermatitis

Warnings

For external use only

Do not use on

- deep or puncture wounds
- animal bites
- serious burns

When using this product

do not get into eyes

Stop use and ask a doctor if

- condition worsens
- symptoms last more than 7 days or clear up and occur again within a few days

Keep out of reach of children.

If swallowed, get medical help or contact a Poison Control Center right away.

Directions

- Open package as designated
- Remove cloths and thoroughly cleanse soiled area
- Apply as needed
- Dispose of cloth in waste receptacle

Other information

- Protect from freezing, avoid excessive heat
- Keep lid tightly sealed
- Not made with natural rubber latex
- Do not flush
- Cloth: made of Rayon/Polyester

Inactive ingredients

Aloe Barbadensis Leaf Juice, Benzalkonium Chloride, Citric Acid, Cocamidopropyl PG-Dimonium Chloride Phosphate, Disodium EDTA, Linoleamidopropyl PG-Dimonium Chloride Phosphate, Simethicone, Sodium Benzoate, Polysorbate 20, Water (Aqua)

Manufacturing Information

www.medline.com
©2012 Medline and Aloetouch are registered trademarks of Medline Industries, Inc.

Manufactured by/Fabriqué par/
Fabricado por:
Medline Industries, Inc.,
Mundelein, IL 60060 USA

Made in USA

To Order Call: 1-800-MEDLINE
RG14DYN